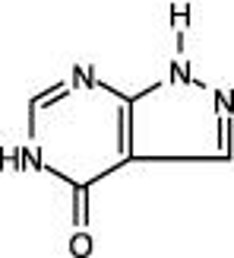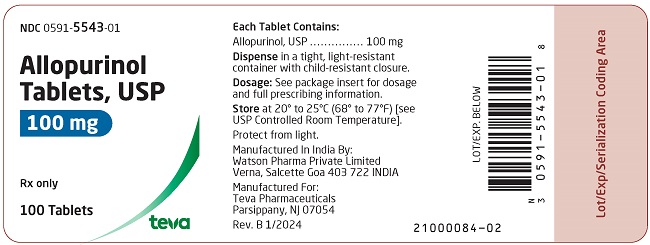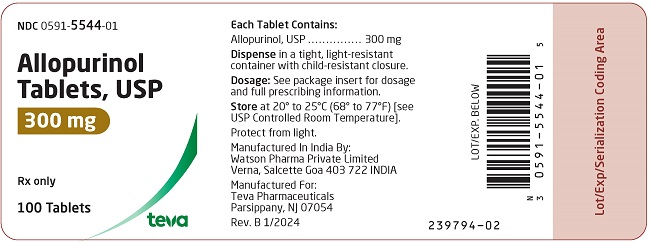 DRUG LABEL: Allopurinol
NDC: 0591-5543 | Form: TABLET
Manufacturer: Actavis Pharma, Inc.
Category: prescription | Type: HUMAN PRESCRIPTION DRUG LABEL
Date: 20240408

ACTIVE INGREDIENTS: ALLOPURINOL 100 mg/1 1
INACTIVE INGREDIENTS: CROSCARMELLOSE SODIUM; LACTOSE MONOHYDRATE; MAGNESIUM STEARATE; CELLULOSE, MICROCRYSTALLINE; STARCH, CORN; SODIUM LAURYL SULFATE

HIGHLIGHTS OF PRESCRIBING INFORMATION

These highlights do not include all the information needed to use ALLOPURINOL TABLETS safely and effectively. See full prescribing information for ALLOPURINOL TABLETS.
ALLOPURINOL tablets, for oral use
Initial U.S. Approval:1966

1 INDICATIONS AND USAGE

Allopurinol Tablets is a xanthine oxidase inhibitor indicated for the management of:

- Adult patients with signs and symptoms of primary or secondary gout (acute attacks, tophi, joint destruction, uric acid lithiasis, and/or nephropathy) (1)
- Adult and pediatric patients with leukemia, lymphoma and solid tumor malignancies who are receiving cancer therapy which causes elevations of serum and urinary uric acid levels (1)
- Adult patients with recurrent calcium oxalate calculi whose daily uric acid excretion exceeds 800 mg/day in male patients and 750 mg/day in female patients, despite lifestyle changes (1)

Limitations of Use

Allopurinol Tablets is not recommended for the treatment of asymptomatic hyperuricemia. (1)

2 DOSAGE AND ADMINISTRATION

- Gout: Prior to initiating treatment assess serum uric acid level, complete blood count, chemistry panel, liver and kidney function tests. Prophylactic treatment for gout flares is recommended. (2.1, 2.2)
  - Patients with normal kidney function: Initial dosage is 100 mg orally daily. Increase by 100 mg weekly increments until serum uric acid of 6 mg/dl or less is reached (maximum 800 mg daily). (2.3)
  - Patients with impaired kidney function: The initial dosage is 50 mg orally daily. Follow recommendations for titration in patients with renal impairment until target serum uric acid level is reached. (2.6)
  - See complete information in the Full Prescribing Information (FPI).
- Hyperuricemia Associated with Cancer Therapy: The recommended dosage is:

- Adults: 300 mg to 800 mg orally daily.
- Pediatric patients: 100 mg/m^2 orally every 8 hours to 12 hours (10 mg/kg/day, maximum 800 mg/day)
- See complete information in the FPI. (2.4, 2.6)

- Recurrent Calcium Oxalate Calculi: The recommended initial dosage in patients with normal kidney function is 200 mg to 300 mg orally daily. (2.5)
- Dosage in Patients with Renal Impairment: See FPI for dosage modifications in patients with renal impairment. (2.6)

3 DOSAGE FORMS AND STRENGTHS

Tablets: 100 mg and 300 mg, scored (3)

4 CONTRAINDICATIONS

Known hypersensitivity to allopurinol or to any of the ingredients of allopurinol tablets. (4)

5 WARNINGS AND PRECAUTIONS

- Skin Rash and Hypersensitivity: Allopurinol has been associated with serious and sometimes fatal dermatological reactions. Discontinue Allopurinol Tablets at the first appearance of skin rash or other signs of hypersensitivity reaction. (5.1)
- Gout Flares: May occur during initiation of treatment. Concurrent prophylactic treatment with colchicine or anti-inflammatory agents is recommended. (5.2)
- Nephrotoxicity: Allopurinol may affect kidney function. Patients with decreased kidney function require lower doses of Allopurinol Tablets. (5.3)
- Hepatoxicity: Cases of reversible hepatotoxicity have occurred. If signs and symptoms of hepatotoxicity develop, evaluate liver function. (5.4)
- Myelosuppression: Bone marrow suppression has been reported with allopurinol. (5.5)
- Potential Effect on Driving and Use of Machinery: Drowsiness, somnolence and dizziness have been reported in patients taking allopurinol. (5.6)

6 ADVERSE REACTIONS

Most common adverse reactions (incidence > 1%) are nausea, diarrhea, and increase in liver function tests. (6)

To report SUSPECTED ADVERSE REACTIONS, contact Teva at 1-888-838-2872 or FDA at 1-800-FDA-1088 or www.fda.gov/medwatch.

7 DRUG INTERACTIONS

- The following drugs may increase the risk of serious skin reactions: bendamustine, thiazide diuretics, ampicillin and amoxicillin. (7.1)
- Capecitabine: Avoid concomitant use. (7.2)
- Mercaptopurine or Azathioprine: Reduce mercaptopurine or azathioprine dose as recommended in the respective prescribing information. (7.2)
- Pegloticase: Discontinue and refrain from initiating treatment with allopurinol tablets. (7.2)
- See FPI for complete list of significant drug interactions. (7.2)

8 USE IN SPECIFIC POPULATIONS

- Pregnancy: May cause fetal harm. (8.1)
- Lactation: Advise not to breastfeed. (8.2)

FULL PRESCRIBING INFORMATION

1 INDICATIONS AND USAGE

Allopurinol Tablets are indicated for:

- The management of adults with signs and symptoms of primary or secondary gout (acute attacks, tophi, joint destruction, uric acid lithiasis, and/or nephropathy)
- The management of adult and pediatric patients with leukemia, lymphoma and solid tumor malignancies who are receiving cancer therapy which causes elevations of serum and urinary uric acid levels
- The management of adult patients with recurrent calcium oxalate calculi whose daily uric acid excretion exceeds 800 mg/day in male patients and 750 mg/day in female patients, despite lifestyle changes (such as reduction of dietary sodium, non-dairy animal protein, oxylate rich foods, refined sugars and increases in oral fluids and fruits and vegetables)

Limitations of Use

Allopurinol Tablets are not recommended for the treatment of asymptomatic hyperuricemia.

2 DOSAGE AND ADMINISTRATION

2.1 Recommended Testing Prior to Treatment Initiation

Prior to initiating treatment with Allopurinol Tablets in patients with gout, assess the following baseline tests: serum uric acid level, complete blood count, chemistry panel, liver function tests (serum alanine aminotransferase [ALT], aspartate aminotransferase [AST], alkaline phosphatase, and total bilirubin), kidney function tests (serum creatinine and eGFR).

2.2 Recommended Prophylaxis for Gout Flares

Gout flares may occur after initiation of Allopurinol Tablets due to changing serum uric acid levels resulting in mobilization of urate from tissue deposits. Flare prophylaxis with colchicine or an anti-inflammatory agent according to practice guidelines is recommended upon initiation of Allopurinol Tablets. While adjusting the dosage of Allopurinol Tablets in patients who are being treated with colchicine and/or anti-inflammatory agents, continue flare prophylaxis drugs until serum uric acid has been normalized and the patient has been free of gout flares for several months. If a gout flare occurs during Allopurinol Treatment, Allopurinol Tablets need not be discontinued. Manage the gout flare concurrently, as appropriate for the individual patient [see Warnings and Precautions (5.2)].

2.3 Recommended Dosage for Gout

The initial recommended dosage for the management of gout is 100 mg orally daily, with weekly increments of 100 mg, until a serum uric acid level of 6 mg/dL or less is reached. Initiating treatment with lower dosages of Allopurinol Tablets and titrating slowly, decreases the risk of gout flares and drug induced serious adverse reactions.

In patients with renal impairment the initial dosage is 50 mg orally daily with lower dose increases until serum uric acid level of 6 mg/dL or less is reached. For complete dosage recommendations for patients with renal impairment see Table 1 [see Dosage and Administration (2.6)].

The minimal effective dosage is 100 mg to 200 mg daily and the maximal recommended dosage is 800 mg daily. The appropriate dosage may be administered in divided doses or as a single equivalent dose with the 300 mg tablet. Doses in excess of 300 mg should be administered in divided doses. Monitor patients’ kidney function during the early stages of administration of Allopurinol Tablets and decrease the dosage or withdraw the drug if persistent abnormalities in kidney function occur [see Dosage and Administration (2.6), Warnings and Precautions (5.3), Use in Specific Populations (8.6)].

The dosage of Allopurinol Tablets to achieve control of gout varies with the severity of the disease. In general, gout control is achieved with 200 mg to 300 mg daily in patients with mild gout, and with 400 mg to 600 mg daily in patients with moderate to severe tophaceous gout. Gout attacks usually become shorter and less severe after several months of therapy.

If a dose of Allopurinol Tablets is missed, there is no need to double the dose at the next scheduled time. Allopurinol Tablets is generally better tolerated if taken following meals. A fluid intake sufficient to yield a daily urinary output of at least 2 liters and the maintenance of a neutral or preferably, slightly alkaline urine are desirable.

Inform patients of the possibility of gout flares [see Warnings and Precautions (5.2)]. Instruct them to remain on Allopurinol Tablets if this occurs and to increase fluid intake during therapy to prevent kidney stones.

Concurrent Use of Uricosuric Agents

Some patients, may benefit using uricosuric agents concurrently, to reduce serum uric acid to target levels.

When transferring a patient from a uricosuric agent to Allopurinol Tablets, reduce the dose of the uricosuric agent over a period of several weeks and increase the dose of Allopurinol Tablets gradually to the required dose needed to maintain target serum uric acid level.

2.4 Recommended Dosage for Hyperuricemia Associated with Cancer Therapy

Initiate therapy with Allopurinol Tablets 24 hours to 48 hours before the start of chemotherapy known to cause tumor cell lysis. Administer fluids sufficient to yield a daily urinary output of at least 2 liters in adults (at least 100 mL/m^2/hour in pediatric patients) with a neutral or, preferably, slightly alkaline urine.

The recommended dosage of Allopurinol Tablets is:

- Adult patients – 300 mg to 800 mg orally daily
- Pediatric patients - 100 mg/m^2 orally every 8 hours to 12 hours (10 mg/kg/day, maximum 800 mg/day). In patients with body surface area < 0.5 m^2, consider using an alternative allopurinol formulation.

The dosage of Allopurinol Tablets to maintain normal or near-normal serum uric acid varies with the severity of the disease. Monitor serum uric acid levels at least daily and administer Allopurinol Tablets at a dose and frequency to maintain the serum uric acid within the normal range. Discontinue Allopurinol Tablets when the risk of tumor lysis has abated (2 days to 3 days from start of chemotherapy). For complete dosage recommendations for patients with renal impairment, see Table 2 [see Dosage and Administration (2.6)].

2.5 Recommended Dosage for Management of Recurrent Calcium Oxalate Calculi in Hyperuricosuric Patients

The recommended dosage for the management of recurrent calcium oxalate stones in hyperuricosuric patients is 200 mg to 300 mg orally daily in divided doses or as the single equivalent. This dose may be adjusted depending upon the resultant control of the hyperuricosuria based upon subsequent 24-hour urinary urate determinations.

2.6 Recommended Dosage in Patients with Renal Impairment

The recommended initial dosages of Allopurinol Tablets in adult patients with renal impairment are shown in Tables 1 and 2 [see Use in Specific Populations (8.6)].

Patients with Gout

The recommended initial dosages in adult patients with gout with impaired kidney function are shown in Table 1 [see Use in Specific Populations (8.6)].

Initiate treatment with a lower dose of Allopurinol Tablets and increase the dose gradually in 50 mg/day increments every 2 weeks to 4 weeks in patients with renal impairment to decrease the risk of drug induced serious adverse reactions. Use the lowest dose possible to achieve the desired effect on serum and/or urine uric acid. Monitor kidney function in gout patients with chronic kidney disease closely when initiating treatment with Allopurinol Tablets and decrease or withdraw the drug if increased abnormalities in kidney function appear and persist.

Table 1. Recommended Initial Dosage in Adult Patients with Gout
eGFR | Initial Dosage
> 60 mL/minute | No dosage modification
> 30 to 60 mL/minute | 50 mg daily
> 15 to 30 mL/minute | 50 mg every other day
5 to 15 mL/minute | 50 mg twice weekly
< 5 mL/minute | 50 mg once weekly

The maximum dosage that should be used in patients with various levels of renal impairment is not defined at different eGFR levels.

Patients with Recurrent Calcium Oxalate Calculi

Data are insufficient to provide dosage recommendations for the treatment of recurrent calcium oxalate calculi in patients with renal impairment. Allopurinol and its metabolites are excreted by the kidney, and accumulation of the drug can occur in renal failure [see Warnings and Precautions (5.3) and Use in Specific Populations (8.6)].

Hyperuricemia Associated with Cancer Therapy

The recommended dosage of Allopurinol Tablets for the management of hyperuricemia associated with cancer therapy in adult patients with renal impairment is shown in Table 2 [see Use in Specific Populations (8.6)].

Table 2. Recommended Dosage of Allopurinol Tablets in Adult Patients for Management of Hyperuricemia Associated with Cancer Therapy with Renal Impairment
eGFR | Recommended Dosage
> 20 mL/min to 60 mL/min | No dosage modification
10 mL/min to 20 mL/min | 200 mg/day
< 10 mL/min | 100 mg/day
On dialysis | 50 mg every 12 hours, or; 100 mg every 24 hours

Treatment with Allopurinol Tablets has not been studied in pediatric patients with severe renal impairment (eGFR < 20 mL/min) or on dialysis. There is insufficient information to establish dosing for Allopurinol Tablets in pediatric patients with renal impairment. In these patients, consider the risks and potential benefits before initiating treatment with Allopurinol Tablets [see Warnings and Precautions (5.3) and Use in Specific Populations (8.6)].

3 DOSAGE FORMS AND STRENGTHS

Allopurinol Tablets, USP are available in the following strengths:

- 100 mg: Round, flat-faced, beveled, scored, white tablets imprinted with “DAN DAN” on one side and “5543” on the other side.
- 300 mg: Round, standard convex, scored, orange tablets imprinted with “DAN DAN” on one side and “5544” on the other side.

4 CONTRAINDICATIONS

Allopurinol Tablets are contraindicated in patients with a history of hypersensitivity reaction to allopurinol or to any of the ingredients of Allopurinol Tablets.

5 WARNINGS AND PRECAUTIONS

5.1 Skin Rash and Hypersensitivity

Serious and sometimes fatal dermatologic reactions, including toxic epidermal necrolysis (TEN), Stevens-Johnson syndrome (SJS), and drug reaction with eosinophilia and systemic symptoms (DRESS) have been reported in patients taking allopurinol [see Adverse Reactions (6)]. These reactions occur in approximately 5 in 10,000 (0.05%) patients taking allopurinol. Other serious hypersensitivity reactions that have been reported include exfoliative, urticarial and purpuric lesions, generalized vasculitis, and irreversible hepatotoxicity. Discontinue Allopurinol Tablets permanently at the first appearance of skin rash or other signs which may indicate a hypersensitivity reaction.

The HLA-B*58:01 allele is a genetic marker for severe skin reactions indicative of hypersensitivity to allopurinol. Patients who carry the HLA-B*58:01 allele are at a higher risk of allopurinol hypersensitivity syndrome (AHS), but hypersensitivity reactions have been reported in patients who do not carry this allele. The frequency of this allele is higher in individuals of African, Asian (e.g., Han Chinese, Korean, Thai), and Native Hawaiian/Pacific Islander ancestry [see Clinical Pharmacology (12.5)]. The use of Allopurinol Tablets is not recommended in HLA- B*58:01 positive patients unless the benefits clearly outweigh the risks.

Consider screening for HLA-B*5801 before starting treatment with Allopurinol Tablets in patients from populations in which the prevalence of this HLA-B*5801 allele is known to be high. Screening is generally not recommended in patients from populations in which the prevalence of HLA-B*58:01 is low, or in current allopurinol users, as the risk of SJS/TEN/DRESS is largely confined to the first few months of therapy, regardless of HLA- B*58:01 status.

Hypersensitivity reactions to Allopurinol Tablets may be increased in patients with decreased kidney function receiving thiazide diuretics and Allopurinol Tablets concurrently. Concomitant use of the following drugs may also increase the risk of skin rash, which may be severe: bendamustine, ampicillin and amoxicillin [see Drug Interactions (7.1)].

Discontinue Allopurinol Tablets immediately if a skin rash develops. Instruct patients to stop taking Allopurinol Tablets immediately and seek medical attention promptly if they develop a rash.

5.2 Gout Flares

Gout flares have been reported during initiation of treatment with Allopurinol Tablets, even when normal or subnormal serum uric acid levels have been attained due to the mobilization of urates from tissue deposits. Even with adequate therapy with Allopurinol Tablets, it may require several months to deplete the uric acid pool sufficiently to achieve control of the flares. The flares typically become shorter and less severe after several months of therapy.

In order to prevent gout flares when treatment with Allopurinol Tablets is initiated, concurrent prophylactic treatment with colchicine or an anti-inflammatory agent is recommended [see Dosage and Administration (2.2)]. Advise patients to continue Allopurinol Tablets and prophylactic treatment even if gout flares occur, as it may take months to achieve control of gout flares.

5.3 Nephrotoxicity

Treatment with Allopurinol Tablets may result in acute kidney injury due to formation of xanthine calculi or due to precipitation of urates in patients receiving concomitant uricosuric agents. Patients with pre-existing kidney disease, including chronic kidney disease or history of kidney stones, may be at increased risk for worsening of kidney function or acute kidney injury due to xanthine calculi while receiving treatment with Allopurinol Tablets.

In patients receiving Allopurinol Tablets for the management of gout or the management of recurrent calcium oxalate calculi, monitor kidney function frequently during the early stages of allopurinol administration. Maintain fluid intake sufficient to yield a urinary output of at least 2 liters per day of neutral or, preferably, slightly alkaline urine to avoid the possibility of formation of xanthine calculi and help prevent renal precipitation of urates in patients receiving concomitant uricosuric agents.

In patients receiving Allopurinol Tablets for the management of tumor lysis syndrome, monitor kidney function at least daily during the early stages of allopurinol administration. Maintain fluid intake sufficient to yield a urinary output of at least 2 liters per day in adults and at least 2 liters/m^2/day (or at least 100 mL/m^2/hour) in pediatric patients [see Dosage and Administration (2.4)].

5.4 Hepatotoxicity

Cases of reversible clinical hepatotoxicity have occurred in patients taking Allopurinol Tablets, and in some patients, asymptomatic rises in serum alkaline phosphatase or serum transaminase have been observed. If anorexia, weight loss, or pruritus develop in patients on Allopurinol Tablets, evaluate liver enzymes. In patients with pre-existing liver disease, monitor liver enzymes periodically. Discontinue Allopurinol Tablets in patients with elevated liver enzymes.

5.5 Myelosuppression

Myelosuppression, manifested by anemia, leukopenia or thrombocytopenia, has been reported in patients receiving Allopurinol Tablets. The cytopenias have occurred as early as 6 weeks up to 6 years after the initiation of therapy of Allopurinol Tablets. Concomitant use of Allopurinol Tablets with cytotoxic drugs associated with myelosuppression may increase the risk of myelosuppression. Monitor blood counts more frequently when cytotoxic drugs are used concomitantly [see Drug Interactions (7.2)].

Concomitant use with allopurinol increases the exposure of either mercaptopurine or azathioprine which may increase the risk of myelosuppression. Reduce the dosage of mercaptopurine or azathioprine as recommended in their respective prescribing information when used concomitantly with Allopurinol Tablets [see Drug Interactions (7.2)].

5.6 Potential Effect on Driving and Use of Machinery

Drowsiness, somnolence and dizziness have been reported in patients taking Allopurinol Tablets [see Adverse Reactions (6)]. Inform patients also that the central nervous system depressant effects of Allopurinol Tablets may be additive to those of alcohol and other CNS depressants.

Advise patients to avoid operation of automobiles or other dangerous machinery and activities made hazardous by decreased alertness when starting Allopurinol Tablets or increasing the dose, until they know how the drug affects them.

6 ADVERSE REACTIONS

The following clinically significant adverse reactions are described elsewhere in the labeling:

- Skin Rash and Hypersensitivity [see Warnings and Precautions (5.1)]
- Nephrotoxicity [see Warnings and Precautions (5.3)]
- Hepatoxicity [see Warnings and Precautions (5.4)]
- Myelosuppression [see Warnings and Precautions (5.5)]
- Potential Effect on Driving and Use of Machinery [see Warnings and Precautions (5.6)]

The following adverse reactions associated with the use of Allopurinol Tablets were identified in literature, unpublished clinical trials or postmarketing reports. Because some of these reactions were reported voluntarily from a population of uncertain size, it is not always possible to reliably estimate their frequency or establish a causal relationship to drug exposure. The most frequent adverse reaction to Allopurinol Tablets is skin rash.

Most Common Adverse Reactions (≥ 1%)

Gastrointestinal: Diarrhea, nausea, alkaline phosphatase increase, AST/ALT increase.

Metabolic and Nutritional: Acute attacks of gout.

Skin and Appendages: Rash, maculopapular rash.

Less Common Adverse Reactions (< 1%)

Body As a Whole: Ecchymosis, fever, headache, malaise.

Cardiovascular: Necrotizing angiitis, vasculitis, pericarditis, peripheral vascular disease, thrombophlebitis, bradycardia, vasodilation.

Gastrointestinal: Hepatic necrosis, granulomatous hepatitis, hepatomegaly, hyperbilirubinemia, cholestatic jaundice, vomiting, intermittent abdominal pain, gastritis, dyspepsia, hemorrhagic pancreatitis, gastrointestinal bleeding, stomatitis, salivary gland swelling, hyperlipidemia, tongue edema, anorexia.

Hemic and Lymphatic: Thrombocytopenia, eosinophilia, leukocytosis, leukopenia, aplastic anemia, agranulocytosis, eosinophilic fibrohistiocytic lesion of bone marrow, pancytopenia, prothrombin decrease, anemia, hemolytic anemia, reticulocytosis, lymphadenopathy, lymphocytosis.

Musculoskeletal: Myopathy, arthralgias, myalgia.

Nervous: Peripheral neuropathy, neuritis, paresthesia, somnolence, optic neuritis, confusion, dizziness, vertigo, foot drop, decrease in libido, depression, amnesia, tinnitus, asthenia, insomnia.

Respiratory: Epistaxis, bronchospasm, asthma, pharyngitis, rhinitis.

Skin and Appendages: Erythema multiforme exudativum (Stevens-Johnson syndrome), toxic epidermal necrolysis (Lyell's syndrome), hypersensitivity vasculitis, purpura, vesicular bullous dermatitis, exfoliative dermatitis, eczematoid dermatitis, pruritus, urticaria, alopecia, onycholysis, lichen planus, furunculosis, facial edema, sweating, skin edema.

Special Senses: Taste loss/perversion, cataracts, macular retinitis, iritis, conjunctivitis, amblyopia.

Urogenital: Renal failure, uremia, nephritis, impotence, primary hematuria, albuminuria.

Endocrine: Infertility (male), hypercalcemia, gynecomastia (male).

7 DRUG INTERACTIONS

7.1 Drugs Known to Affect the Occurrence of Skin Rash and Hypersensitivity

Concomitant use of the following drugs may increase the risk of skin rash, which may be severe: bendamustine, thiazide diuretics, ampicillin and amoxicillin. Renal impairment may further increase risk with concomitant use of thiazide diuretics [see Warnings and Precautions (5.1, 5.2) and Clinical Pharmacology (12.2)].

Monitor kidney function and reduce the dose of Allopurinol Tablets in patients with concomitant thiazide diuretic use and impaired renal function [see Dosage and Administration (2.6), Warnings and Precautions (5.1)].

Discontinue Allopurinol Tablets at the first appearance of skin rash or other signs which may indicate a hypersensitivity reaction when use concomitantly with these drugs [see Warnings and Precautions (5.1)].

7.2 Drugs Known to Have Clinically Important Drug Interactions with Allopurinol Tablets

Table 3: Interventions for Clinically Important Drug Interactions with Allopurinol Tablets
Capecitabine
Clinical Impact | Concomitant use with allopurinol may decrease concentration of capecitabine’s active metabolites, which may decrease capecitabine efficacy.
Intervention | Avoid the use of Allopurinol Tablets during treatment with capecitabine
Chlorpropamide
Clinical Impact | Allopurinol prolongs the half-life of chlorpropamide as both compete for renal tubular excretion. In patients with renal insufficiency, the risk of hypoglycemia may be increased due to this mechanism.
Intervention | Monitor patients with renal insufficiency for hypoglycemia when administering chlorpropamide and Allopurinol Tablets concomitantly.
Cyclosporine
Clinical Impact | Concomitant use of allopurinol increases cyclosporine concentrations, which may increase the risk of adverse reactions.
Intervention | Increase frequency of monitoring cyclosporine concentrations as reflected in its prescribing information and modify the dosage of cyclosporine as appropriate when used concomitantly with Allopurinol Tablets.
Cyclophosphamide and Other Cytotoxic Agents
Clinical Impact | Concomitant use of allopurinol with cyclophosphamide and other cytotoxic agents (doxorubicin, bleomycin, procarbazine, mechloroethamine) increases bone marrow suppression among patients with neoplastic disease, except leukemia.
Intervention | Blood count monitoring and regular physician follow-up are recommended.
Dicumarol
Clinical Impact | Allopurinol prolongs the half-life of the anticoagulant, dicumarol. The mechanism of this drug interaction has not been established but should be noted when Allopurinol Tablets is given to patients already on dicumarol therapy.
Intervention | Monitor prothrombin time. Adjust the dosage of dicumarol accordingly when Allopurinol Tablets is added to anticoagulant therapy.
Fluorouracil
Clinical Impact | Based on non-clinical data, allopurinol may decrease anti-tumor activity due to suppression of phosphorylation of 5-fluorouracil.
Intervention | Concomitant administration with fluorouracil should be avoided.
Mercaptopurine or Azathioprine
Clinical Impact | Allopurinol inhibits xanthine oxidase mediated metabolism of mercaptopurine and azathioprine. Concomitant use of allopurinol increases the exposure of either mercaptopurine or azathioprine which may increase the risk of their adverse reactions, including myelosuppression [see Warnings and Precautions 5.5].
Intervention | In patients receiving mercaptopurine or azathioprine, the concomitant administration of 300 mg to 600 mg of Allopurinol Tablets per day will require a reduction in dose to approximately one third to one fourth of the usual dose of mercaptopurine or azathioprine. Subsequent adjustment of doses of mercaptopurine or azathioprine should be made on the basis of therapeutic response and the appearance of toxic effects.
Pegloticase
Clinical Impact | Concomitant use of allopurinol and pegloticase may potentially blunt the rise of serum uric acid levels and increase the risk of pegloticase related anaphylaxis in patients whose uric acid level increase to above 6 mg/dL.
Intervention | Discontinue and do not institute therapy with Allopurinol Tablets during treatment with pegloticase.
Theophylline
Clinical Impact | Concomitant use of allopurinol doses greater than or equal to 600 mg/day may decrease the clearance of theophylline
Intervention | Monitor and adjust theophylline doses as reflected in the prescribing information.
Uricosuric Drugs
Clinical Impact | Uricosuric agents increase the excretion of the active allopurinol metabolite oxypurinol. Concomitant use with uricosuric agents decreases oxypurinol exposure which may reduce the inhibition of xanthine oxidase by oxypurinol and increases the urinary excretion of uric acid.; The net effect of such combined therapy may be useful in some patients in achieving minimum serum uric acid levels provided the total urinary uric acid load does not exceed the competence of the patient's kidney function.
Intervention | Monitor uric acid levels due to the increased chance of hypouricemic effects.
Warfarin
Clinical Impact | Allopurinol may inhibit the metabolism of warfarin, possibly enhancing its anticoagulant effect.
Intervention | Monitor patients on concomitant therapy for excessive anticoagulation. Assess INR frequently and adjust warfarin dosage accordingly when allopurinol is added to warfarin therapy.

8 USE IN SPECIFIC POPULATIONS

8.1 Pregnancy

Risk Summary

Based on findings in animals, Allopurinol Tablets may cause fetal harm when administered to a pregnant woman. Adverse developmental outcomes have been described in exposed animals (see Data). Allopurinol and its metabolite oxypurinol have been shown to cross the placenta following administration of maternal allopurinol.

Available limited published data on allopurinol use in pregnant women do not demonstrate a clear pattern or increase in frequency of adverse developmental outcomes. Among approximately 50 pregnancies described in published literature, 2 infants with major congenital malformations have been reported with following maternal allopurinol exposure. Advise pregnant women of the potential risk to a fetus.

All pregnancies have a background risk of birth defect, loss, or other adverse outcomes. The background risk of major birth defects and miscarriage for the indicated population is unknown.

In the U.S. general population, the estimated background risk of major birth defects and miscarriage in clinically recognized pregnancies is 2% to 4% and 15% to 20%, respectively.

Data

Human Data

Experience with Allopurinol Tablets during human pregnancy has been limited partly because women of reproductive age rarely require treatment with Allopurinol Tablets. A case report published in 2011 described the outcome of a full-term pregnancy in a 35-year-old woman who had recurrent kidney stones since age 18 who took allopurinol throughout the pregnancy. The child had multiple complex birth defects and died at 8 days of life. A second report in 2013 provided data on 31 prospectively ascertained pregnancies involving mothers exposed to allopurinol for varying durations during the first trimester. The overall rate of major fetal malformations and spontaneous abortions was reported to be within the normal expected range; however, one child had severe malformations similar to those described in the cited earlier case report.

Animal Data

There was no evidence of fetotoxicity or teratogenicity in rats or rabbits treated during the period of organogenesis with oral allopurinol at doses up to 200 mg/kg/day and up to 100 mg/kg/day, respectively (about 2.4 times the human dose on a mg/m^2 basis). However, there is a published report in pregnant mice that single intraperitoneal doses of 50 mg/kg or 100 mg/kg (about 0.3 or 0.6 times the human dose on a mg/m^2 basis) of allopurinol on gestation days 10 or 13 produced significant increases in fetal deaths and teratogenic effects (cleft palate, harelip, and digital defects). It is uncertain whether these findings represented a fetal effect or an effect secondary to maternal toxicity.

8.2 Lactation

Risk Summary

Allopurinol and oxypurinol are present in human milk. Based on information from a single case report, allopurinol and its active metabolite, oxypurinol, were detected in the milk of a mother receiving 300 mg of allopurinol daily at 5 weeks postpartum. The estimated relative infant dose were 0.14 mg/kg and 0.2 mg/kg of allopurinol and between 7.2 mg/kg to 8 mg/kg of oxypurinol daily. There was no report of effects of allopurinol on the breastfed infant or on milk production. Because of the potential for serious adverse reactions in a breastfed child, advise women not to breastfeed during treatments with Allopurinol Tablets and for one week after the last dose.

8.4 Pediatric Use

Hyperuricemia Associated with Cancer Therapy

The safety and effectiveness of allopurinol for the management of pediatric patients with leukemia, lymphoma and solid tumor malignancies who are receiving cancer therapy which causes elevations of serum and urinary uric acid levels have been established in approximately 200 pediatric patients. The efficacy and safety profile observed in this patient population were similar to that observed in adults.

Primary or Secondary Gout

The safety and effectiveness of Allopurinol Tablets have not been established for the treatment of signs and symptoms of primary or secondary gout in pediatric patients.

Recurrent Calcium Oxalate Calculi

The safety and effectiveness of Allopurinol Tablets have not been established for the management of pediatric patients with recurrent calcium oxalate calculi.

Inborn Errors of Metabolism

The safety and effectiveness of Allopurinol Tablets have not been established in pediatric patients with rare inborn errors of purine metabolism.

8.6 Renal Impairment

Allopurinol and its primary active metabolite, oxipurinol, are eliminated by the kidneys; therefore, changes in renal function have a profound effect on exposure. In patients with decreased renal function or who have concurrent illnesses which can affect renal function, perform periodic laboratory parameters of renal function and reassess the patient's dosage of Allopurinol Tablets [see Dosage and Administration (2.6), Warnings and Precautions (5.3)].

10 OVERDOSAGE

In the management of overdosage there is no specific antidote for Allopurinol Tablets. Both allopurinol and oxipurinol are dialyzable; however, the usefulness of hemodialysis or peritoneal dialysis in the management of an overdose of Allopurinol Tablets is unknown.

11 DESCRIPTION

Allopurinol, USP is a xanthine oxidase inhibitor. It has the following structural formula:

Allopurinol, USP is known chemically as 1, 5-dihydro-4H-pyrazolo [3, 4-d]pyrimidin-4-one and it has a molecular weight of 136.11 g/mol. Its solubility in water at 37°C is 80.0 mg/dL and is greater in an alkaline solution. It is a xanthine oxidase inhibitor which is administered orally.

Allopurinol Tablets USP, 100 mg and 300 mg contain the following inactive ingredients: croscarmellose sodium, lactose monohydrate, magnesium stearate, microcrystalline cellulose, pregelatinized corn starch and sodium lauryl sulfate. In addition, the 300 mg strength also contains FD&C Yellow No. 6.

12 CLINICAL PHARMACOLOGY

12.1 Mechanism of Action

Allopurinol is a structural analogue of the natural purine base, hypoxanthine.

Allopurinol acts on purine catabolism, without disrupting the biosynthesis of purines. It reduces the production of uric acid by inhibiting the biochemical reactions immediately preceding its formation. It is an inhibitor of xanthine oxidase, the enzyme responsible for the conversion of hypoxanthine to xanthine and of xanthine to uric acid, the end product of purine metabolism in humans. Allopurinol is metabolized to the corresponding xanthine analogue, oxypurinol (alloxanthine), which also is an inhibitor of xanthine oxidase.

12.2 Pharmacodynamics

Allopurinol reduces the production of uric acid by inhibiting the biochemical reactions immediately preceding its formation in a dose dependent manner. The pharmacological action of allopurinol is generally believed to be mediated by its oxypurinol metabolite.

Effect on Hypoxanthine and Xanthine

Reutilization of both hypoxanthine and xanthine for nucleotide and nucleic acid synthesis is markedly enhanced when their oxidations are inhibited by allopurinol and oxipurinol. This reutilization does not disrupt normal nucleic acid anabolism, however, because feedback inhibition is an integral part of purine biosynthesis. As a result of xanthine oxidase inhibition, the serum concentration of hypoxanthine plus xanthine in patients receiving allopurinol for treatment of hyperuricemia is usually in the range of 0.3 mg/dL to 0.4 mg/dL compared to a normal level of approximately 0.15 mg/dL. A maximum of 0.9 mg/dL of these oxypurines has been reported when the serum urate was lowered to less than 2 mg/dL by high doses of allopurinol. These values are far below the saturation levels at which point their precipitation would be expected to occur (above 7 mg/dL). The increased xanthine and hypoxanthine in the urine in patients who were treated with oral allopurinol have not been accompanied by problems of nephrolithiasis; however, there are isolated case reports of xanthine crystalluria.

Drug Interaction Studies

Fluorouracil: Based on non-clinical data, allopurinol may decrease anti-tumor activity due to suppression of phosphorylation of 5-fluorouracil.

Pegloticase: Concomitant use of allopurinol and pegloticase may potentially blunt the rise of serum uric acid levels required for monitoring the safe use of pegloticase.

Cytotoxic Agents: Enhanced bone marrow suppression by cyclophosphamide and other cytotoxic agents has been reported among patients with neoplastic disease, except leukemia, in the presence of allopurinol.

Thiazide Diuretics: Reports that the concomitant administration of allopurinol and thiazide diuretics contributed to increased allopurinol toxicity were reviewed; however, a causal mechanism or cause-and-effect relationship was not found.

12.3 Pharmacokinetics

Absorption

Allopurinol is approximately 90% absorbed from the gastrointestinal tract. Peak plasma levels generally occur at 1.5 hours and 4.5 hours for allopurinol and oxipurinol respectively. After a single oral dose of 300 mg allopurinol, maximum plasma levels of about 3 mcg/mL of allopurinol and 6.5 mcg/mL of oxipurinol are produced.

Elimination

The half-life of allopurinol and oxipurinol are approximately 1 hour to 2 hours and 15 hours following oral dose of allopurinol, respectively.

Metabolism

Allopurinol is metabolized to the corresponding xanthine analogue, oxypurinol (alloxanthine), which also is an inhibitor of xanthine oxidase.

Excretion

Allopurinol and its primary active metabolite, oxipurinol, are eliminated by the kidneys. Approximately 20% of the ingested allopurinol is excreted in the feces. Oxipurinol is primarily eliminated unchanged in urine by glomerular filtration and tubular reabsorption.

Drug Interaction Studies

Capecitabine: Concomitant use with allopurinol may decrease concentration of capecitabine’s active metabolites, which may decrease capecitabine efficacy.

Cyclosporine: Concomitant use of allopurinol increases cyclosporine concentrations which may increase the risk of adverse reactions.

Mercaptopurine or Azathioprine: Allopurinol inhibits xanthine oxidase mediated metabolism of mercaptopurine and azathioprine. Concomitant use of allopurinol increases the exposure of either mercaptopurine or azathioprine which may increase the risk of their adverse reactions including myelosuppression.

Theophylline: Concomitant use of allopurinol doses greater than or equal to 600 mg/day may decrease the clearance of theophylline.

Uricosuric Agents: Uricosuric agents increase the excretion of the active allopurinol metabolite oxypurinol. Concomitant use with uricosuric agents decreases oxypurinol exposure which may reduce the inhibition of xanthine oxidase by oxypurinol and increases the urinary excretion of uric acid.

Warfarin: Allopurinol may inhibit the metabolism of warfarin, possibly enhancing its anticoagulant effect.

12.5 Pharmacogenomics

HLA-B*5801 allele

The HLA-B*5801 allele is a genetic marker that has shown to be associated with risk of developing allopurinol related hypersensitivity syndrome (DRESS) and SJS/TEN. The frequency of the HLA- B*58:01 allele ranges from 8 to 10% in Han Chinese populations, about 8% in Thai populations, and about 6% in Korean populations based upon published literature and available databases. The frequency of the HLA-B*58:01 allele is about 4% in Blacks, about 1 % to 2 % in indigenous peoples of the Americas and Hispanic populations, and < 1% in people from European descent and Japanese.

Stevens-Johnson syndrome (SJS)/Toxic epidermal necrolysis (TEN) can still occur in patients who are found to be negative for HLA-B*5801 irrespective of ethnic origin.

13 NONCLINICAL TOXICOLOGY

13.1 Carcinogenesis, Mutagenesis, Impairment of Fertility

No evidence of tumorigenicity was observed in male or female mice or rats that received oral allopurinol for the majority of their life spans (greater than 88 weeks) at doses up to 20 mg/kg/day (0.1 and 0.2 times the MRHD on a mg/m^2 basis in mice and rats, respectively).

Allopurinol tested negative in the following genotoxicity assays: the in vitro Ames assay, in vitro mouse lymphoma assay, and in vivo rat bone marrow micronucleus assay. Allopurinol administered intravenously to rats (50 mg/kg) was not incorporated into rapidly replicating intestinal DNA. No evidence of clastogenicity was observed in lymphocytes taken from patients treated with allopurinol (mean duration of treatment 40 months), or in an in vitro assay with human lymphocytes.

Allopurinol oral doses of 20 mg/kg/day had no effect on male or female fertility in rats or rabbits (approximately 0.2 or 0.5 times the MRHD on a mg/m^2 basis, respectively).

16 HOW SUPPLIED/STORAGE AND HANDLING

How Supplied

Allopurinol Tablets is available in multiple tablet strengths and package sizes (bottles with child-resistant caps) as listed in Table 4.

TABLE 4: Allopurinol Tablet Presentations
Tablet Strength | Tablet Description | Package Sizes (NDC)
100 mg | Round, flat-faced, beveled, scored, white tablets imprinted with “DAN DAN” on one side and “5543” on the other side | Bottles of:; - 100 tablets (NDC 0591-5543-01) - 1,000 tablets (NDC 0591-5543-10)
300 mg | Round, standard convex, scored, orange tablets imprinted with “DAN DAN” on one side and “5544” on the other side | Bottles of:; - 100 tablets (NDC 0591-5544-01) - 500 tablets (NDC 0591-5544-05)

Storage and Handling

Store at 20°C to 25°C (68°F to 77°F) [See USP Controlled Room Temperature]. Protect from light.

Dispense in a tight, light-resistant container with child-resistant closure.

17 PATIENT COUNSELING INFORMATION

Administration

Advise patients to take Allopurinol Tablets after meals to minimize gastric irritation. If a single dose of allopurinol tablets is occasionally forgotten, there is no need to double the dose at the next scheduled time.

Skin Rash and Hypersensitivity

Inform patients that Allopurinol Tablets may increase the risk of serious and sometimes fatal dermatologic reactions. Instruct patients to discontinue Allopurinol Tablets and to seek medical attention immediately, at the first sign of a skin rash, blisters, fever, painful urination, blood in the urine, irritation of the eyes, swelling of the lips or mouth, or other signs and symptoms of hypersensitivity reactions [see Warnings and Precautions (5.1)].

Gout Flares During Treatment with Allopurinol Tablets

Inform patients that gout flares may occur during initiation of treatment with Allopurinol Tablets, even when their serum uric acid is normal. Concurrent use of additional medications such as colchicine or other anti-inflammatory agents can prevent gout flares. Advise patients to continue treatment with both, Allopurinol Tablets and the prophylactic therapy as prescribed, even if gout flares occur. Reassure them that it may take months to achieve control of the flares but the flares typically become shorter and less severe after several months of therapy [see Warnings and Precautions (5.2)].

Nephrotoxicity

Inform patients that Allopurinol Tablets may affect kidney function. Advise them to increase fluid intake during therapy (i.e., for adults, at least 2 liters of liquids per day) and to stay well hydrated to prevent kidney stones [see Warnings and Precautions (5.3)].

Hepatotoxicity

Inform patients of the risk of hepatotoxicity and to report to their healthcare provider any signs and symptoms of liver failure, including jaundice, pruritus, bleeding, bruising, or anorexia [see Warnings and Precautions (5.4)].

Myelosuppression

Advise patients of the risk of myelosuppression and to report any signs and symptoms of infection, fever, bleeding, shortness of breath, or significant fatigue to their healthcare provider [see Warnings and Precautions (5.5)].

Potential Effect on Driving and Use of Machinery

Inform patients that drowsiness, somnolence and dizziness have been reported in patients taking Allopurinol Tablets. Inform also that the central nervous system depressant effects of Allopurinol Tablets may be additive to those of alcohol and other CNS depressants. Advise patients to avoid operation of automobiles or other dangerous machinery and activities made hazardous by decreased alertness when starting Allopurinol Tablets or increasing the dose, until they know how the drug affects them [see Warnings and Precautions (5.6)].

Risks Associated with Use of Concomitant Medications

Inform patients that there are risks of adverse effects when Allopurinol Tablets are used with the following drugs: dicumarol, warfarin, sulfinpyrazone, mercaptopurine, azathioprine, ampicillin, amoxicillin, pegloticase, theophylline, and thiazide diuretics. Advise patients to disclose all medications in use and they should follow the instructions of their physician [see Drug Interactions (7.2)].

Pregnancy

Advise pregnant women of the potential risk to a fetus. Advise women to notify their healthcare provider if they become pregnant or intend to become pregnant during treatment with Allopurinol Tablets [see Use in Specific Populations (8.1)].

Lactation

Advise women not to breastfeed during treatment with Allopurinol Tablets and for one week after the last dose [see Use in Specific Populations (8.2)].

Manufactured In India By:
Watson Pharma Private Limited
Verna, Salcette Goa 403 722 INDIA

Manufactured For:

Teva Pharmaceuticals

Parsippany, NJ 07054

Rev. C 4/2024

PRINCIPAL DISPLAY PANEL

NDC 0591-5543-01
Allopurinol
Tablets, USP
100 mg
100 Tablets
Rx only

PRINCIPAL DISPLAY PANEL

NDC 0591-5544-01
Allopurinol
Tablets, USP
300 mg
100 Tablets
Rx only